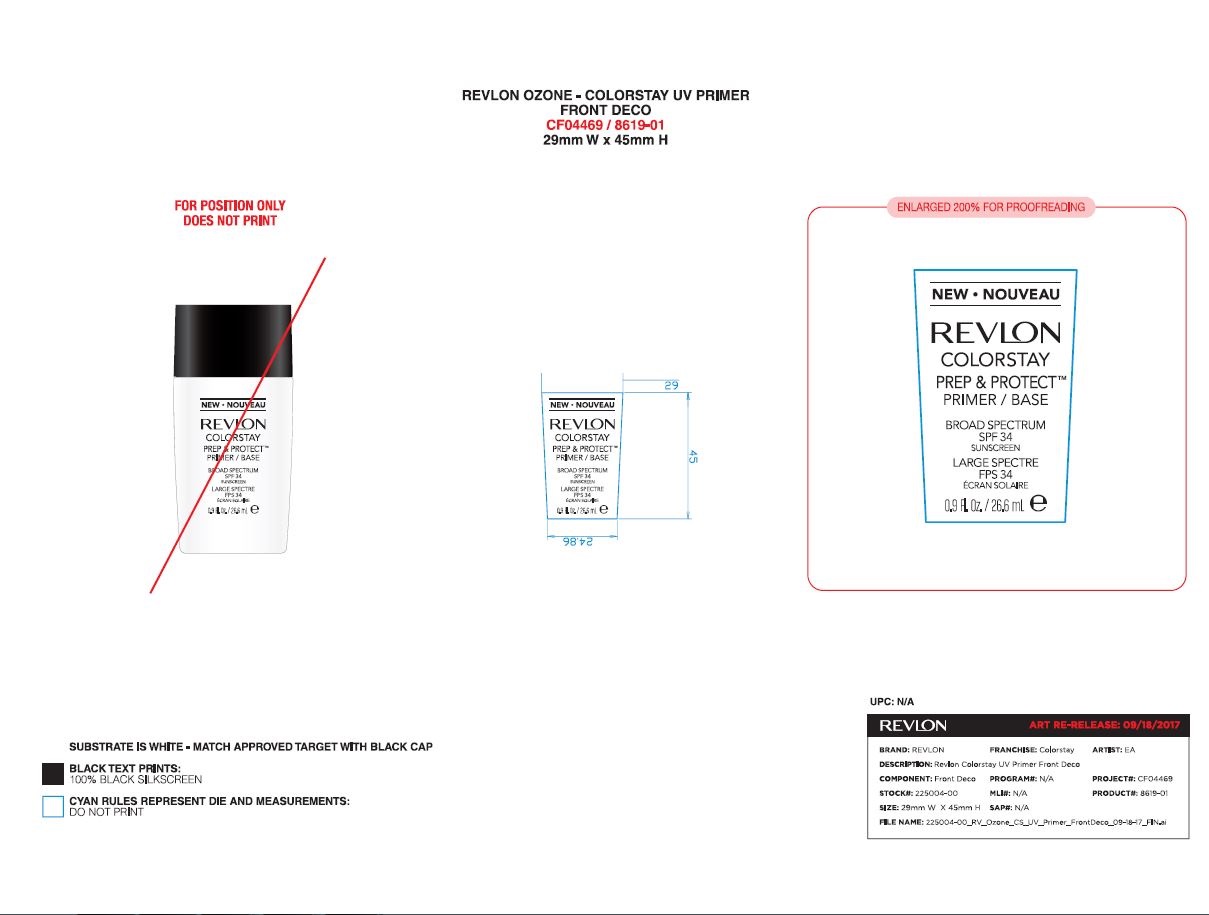 DRUG LABEL: Revlon Colorstay Preo and Protect Primer
NDC: 10967-652 | Form: LIQUID
Manufacturer: Revlon Consumer Products Corp
Category: otc | Type: HUMAN OTC DRUG LABEL
Date: 20241231

ACTIVE INGREDIENTS: ZINC OXIDE 9 mg/1 mL; OCTINOXATE 7.5 mg/1 mL; TITANIUM DIOXIDE 3.6 mg/1 mL
INACTIVE INGREDIENTS: GLYCERIN; PEG-10 DIMETHICONE (600 CST); CYCLOMETHICONE 5; HEXAMETHYLENE DIISOCYANATE/TRIMETHYLOL HEXYLLACTONE CROSSPOLYMER; PERLITE; PEG-12 DIMETHICONE/PPG-20 CROSSPOLYMER; XANTHAN GUM; DIMETHICONE/VINYL DIMETHICONE CROSSPOLYMER (SOFT PARTICLE); SODIUM LACTATE; ALUMINUM OXIDE; TRIMETHYLSILOXYSILICATE (M/Q 0.6-0.8); HEXYL LAURATE; 1,2-HEXANEDIOL; BROWN IRON OXIDE; MAGNESIUM SULFATE, UNSPECIFIED; WATERMELON; APPLE; ALPHA-TOCOPHEROL ACETATE; PHENOXYETHANOL; EDETATE SODIUM; WATER; PEG-9 POLYDIMETHYLSILOXYETHYL DIMETHICONE; DIMETHICONE; POLYMETHYLSILSESQUIOXANE (4.5 MICRONS); POLYGLYCERYL-4 ISOSTEARATE; STEARIC ACID; CAPRYLYL GLYCOL; LENS CULINARIS FRUIT; SALICYLIC ACID; SODIUM PYRROLIDONE CARBOXYLATE; ETHYLHEXYL PALMITATE; BUTYLENE GLYCOL; SILICA DIMETHYL SILYLATE

Revlon Colorstay Prep & Protect Primer / Base

Active Ingredients

Titanium Dioxide 3.6%

Zinc Oxide 9.0%

Octinoxate 7.5%

Purpose

Sunscreen

Warnings

For external use only.

Do not use on damaged or broken skin.

When using this product keep out of eyes. Rinse with water to remove.

Stop use and ask a doctor if rash occurs.

Keep out of reach of children.

If swollowed, get medical help or contact a Poison Control Center right away.

Directions

Apply liberally 15 minutes before sun exposure.

Repply at least every 2 hours.

Use a water resistant sunscreen when swimming or sweating

Sun Protection Measures

Spending time in the sun increases your risk of skin cancer and early skin aging. To decrease the risk, regularly us sunscreen with a Broad Spectrum SPF value of 15 or higher and other sun proection measures including:

- limit time in the sun, especially from 10a.m - 2p.m.

- wear long -sleeved shirts, pants, hats and sunglasses.

- children under 6 months: Ask a doctor

Inactive Ingredients

CYCLOPENTASILOXANE; AQUA/WATER/EAU; ZINC OXIDE ; ETHYLHEXYL METHOXYCINNAMATE; TRIMETHYLSILOXYSILICATE; GLYCERIN; TITANIUM DIOXIDE; PEG-10 DIMETHICONE; PEG-9 POLYDIMETHYLSILOXYETHYL DIMETHICONE; DIMETHICONE; POLYMETHYLSILSESQUIOXANE; HDI/TRIMETHYLOL HEXYLLACTONE CROSSPOLYMER]; HEXYL LAURATE; POLYGLYCERYL-4 ISOSTEARATE; PERLITE; DIMETHICONE/PEG-10/15 CROSSPOLYMER; PHENOXYETHANOL; XANTHAN GUM; MAGNESIUM SULFATE; STEARIC ACID; CAPRYLYL GLYCOL; 1,2-HEXANEDIOL; ALUMINA; CITRULLUS LANATUS (WATERMELON) FRUIT EXTRACT]; LENS ESCULENTA (LENTIL) FRUIT EXTRACT; POLYSILICONE-11; PYRUS MALUS (APPLE) FRUIT EXTRACT; IRON OXIDES (CI 77499); TOCOPHERYL ACETATE; SODIUM LACTATE; SODIUM PCA; TETRASODIUM EDTA; ETHYLHEXYL PALMITATE; BUTYLENE GLYCOL; SALICYLIC ACID; SILICA DIMETHYL SILYLATE

DOSAGE AND ADMINISTRATION

Apply liberally 15 minutes before sun exposure.

INDICATIONS AND USAGE

Helps prevent sunbunrs. If used as directed with other sun protection measures (See Directions), decreases the risk of skin cancer and early skin aging caused by the sun.

KEEP OUT OF REACH OF CHILDREN

Keep out of the reach of children. If product is swallowed, get medical help or contact a Poison Control Center right away.

Principal Display Panel

REVLON

Colorstay Prep & Protect Primer / Base